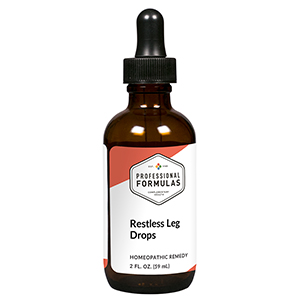 DRUG LABEL: Restless Leg Drops
NDC: 63083-2172 | Form: LIQUID
Manufacturer: Professional Complementary Health Formulas
Category: homeopathic | Type: HUMAN OTC DRUG LABEL
Date: 20190815

ACTIVE INGREDIENTS: PSEUDOGNAPHALIUM OBTUSIFOLIUM WHOLE 4 [hp_X]/59 mL; AVISCUMINE 4 [hp_X]/59 mL; ACONITUM NAPELLUS WHOLE 6 [hp_X]/59 mL; STRYCHNOS IGNATII SEED 6 [hp_X]/59 mL; RHODODENDRON TOMENTOSUM LEAFY TWIG 6 [hp_X]/59 mL; TOXICODENDRON PUBESCENS LEAF 6 [hp_X]/59 mL; SULFUR 6 [hp_X]/59 mL; MAGNESIUM PHOSPHATE, DIBASIC TRIHYDRATE 8 [hp_X]/59 mL; ARSENIC TRIOXIDE 12 [hp_X]/59 mL; CAUSTICUM 12 [hp_X]/59 mL; ZINC 12 [hp_X]/59 mL
INACTIVE INGREDIENTS: ALCOHOL; WATER

C172

ACTIVE INGREDIENTS

Gnaphalium polycephalum 4X
Viscum album 4X
Aconitum napellus 6X
Ignatia amara 6X
Ledum palustre 6X
Rhus toxicodendron 6X
Sulphur 6X, 12X
Magnesia phosphorica 8X
Arsenicum album 12X
Causticum 12X
Zincum metallicum 12X

QUESTIONS

Professional Formulas

PO Box 2034 Lake Oswego, OR 97035

INDICATIONS

For temporary relief of itching or tingling legs, or an impulse to move legs.*

PURPOSE

*Claims based on traditional homeopathic practice, not accepted medical evidence. Not FDA evaluated.

WARNINGS

Consult a doctor if condition worsens or if symptoms persist. Keep out of the reach of children. In case of overdose, get medical help or contact a poison control center right away. If pregnant or breastfeeding, ask a healthcare professional before use.

Keep out of the reach of children.

PREGNANCY OR BREAST FEEDING

If pregnant or breastfeeding, ask a healthcare professional before use.

DIRECTIONS

Place drops under tongue 30 minutes before/after meals. Adults and children 12 years and over: Take 10 drops up to 3 times per day for up to 6 weeks. For immediate onset of symptoms, take 10 to 15 drops every 15 minutes up to 3 hours. For less severe symptoms, take 10-15 drops hourly up to 8 hours. Consult a physician for use in children under 12 years of age.

OTHER INFORMATION

Tamper resistant. If seal is broken, do not use. After opening, close container tightly and store at room temperature away from heat.

INACTIVE INGREDIENTS

20% ethanol, purified water.

LABEL

Est 1985

Professional Formulas

Complementary Health

Restless Leg Drops

Homeopathic Remedy

2 FL. OZ. (59 mL)